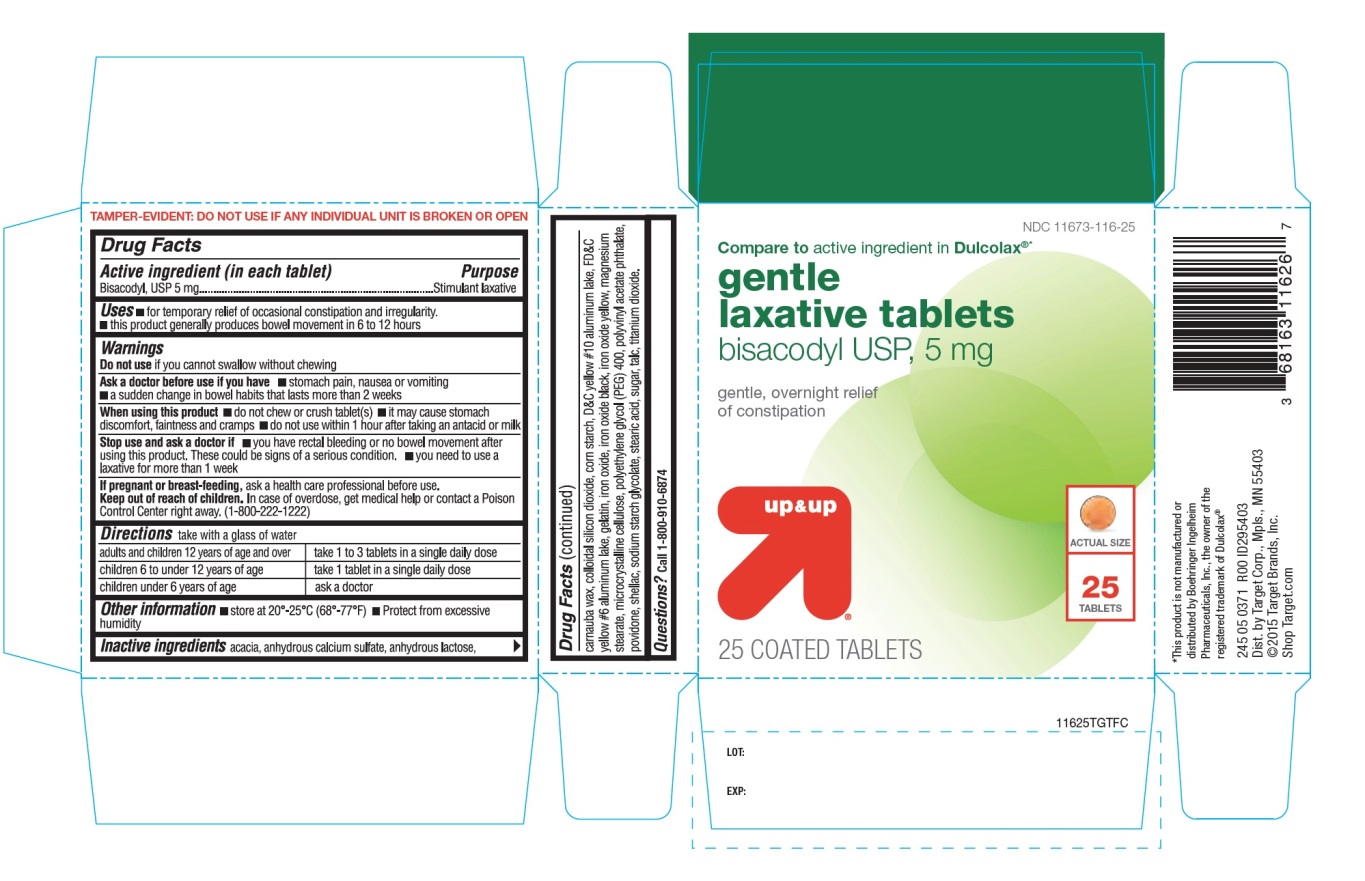 DRUG LABEL: up and up gentle laxative
NDC: 11673-116 | Form: TABLET, COATED
Manufacturer: Target Corporation
Category: otc | Type: HUMAN OTC DRUG LABEL
Date: 20251104

ACTIVE INGREDIENTS: BISACODYL 5 mg/1 1
INACTIVE INGREDIENTS: ACACIA; CALCIUM SULFATE ANHYDROUS; ANHYDROUS LACTOSE; CARNAUBA WAX; SILICON DIOXIDE; STARCH, CORN; D&C YELLOW NO. 10; FD&C YELLOW NO. 6; GELATIN, UNSPECIFIED; FERROUS OXIDE; FERROSOFERRIC OXIDE; FERRIC OXIDE YELLOW; MAGNESIUM STEARATE; MICROCRYSTALLINE CELLULOSE; POLYVINYL ACETATE PHTHALATE; POVIDONE, UNSPECIFIED; POLYETHYLENE GLYCOL 400; SHELLAC; SODIUM STARCH GLYCOLATE TYPE A CORN; STEARIC ACID; SUCROSE; TALC; TITANIUM DIOXIDE

up and up gentle laxative tablets

Active ingredient (in each tablet)

Bisacodyl, USP 5 mg

Purpose

Stimulant laxative

Uses

- for temporary relief of occasional constipation and irregularity
- this product generally produces bowel movement in 6 to 12 hours

Warnings

Do not use

if you cannot swallow without chewing

Ask a doctor before use if you have

- stomach pain, nausea or vomiting
- a sudden change in bowel habits that lasts more than 2 weeks

When using this product

- do not chew or crush tablet(s)
- it may cause stomach discomfort, faintness and cramps
- do not use within 1 hour after taking an antacid or milk

Stop use and ask a doctor if

- you have rectal bleeding or no bowel movement after using this product. These could be signs of a serious condition.
- you need to use a laxative for more than 1 week

If pregnant or breast-feeding,

ask a health professional before use

Keep out of reach of children.

In case of overdose, get medical help or contact a Poison Control Center right away. (1-800-222-1222)

Directions

take with a glass of water

adults and children 12 years of age and over | take 1 to 3 tablets in a single daily dose
children 6 to under 12 years of age | take 1 tablet in a single daily dose
children under 6 years of age | ask a doctor

Other information

- store at 20°-25°C (68°-77°F)
- Protect from excessive humidity

Inactive ingredients

acacia, anhydrous calcium sulfate, anhydrous lactose, carnauba wax, colloidal silicon dioxide, corn starch, D&C yellow #10 aluminum lake, FD&C yellow #6 aluminum lake, gelatin, iron oxide, iron oxide black, iron oxide yellow, magnesium stearate, microcrystalline cellulose, polyethylene glycol (PEG)400, polyvinyl acetate phthalate, povidone, shellac, sodium starch glycolate, stearic acid, sugar, talc, titanium dioxide.

Questions?

Call 1-800-910-6874

Principal Display Panel

NDC 11673-116-25

Compareto active ingredient in Dulcolax®*

gentle laxative tablets

bisacodyl USP, 5 mg

gentle, overnight relief of constipation

25 Tablets

25 COATED TABLETS

*This product is not manufactured or distributed by Boehringer Ingelheim Pharmaceuticals, Inc., the owner of the registered trademark of Dulcolax®

245 05 0371 R00 ID295403

Dist.by Target Corp., Mpls., MN 55403

©2015 Target Brands, Inc.

Shop Target.com

TAMPER- EVIDENT: DO NOT USE IF ANY INDIVIDUAL UNIT IS BROKEN OR OPEN